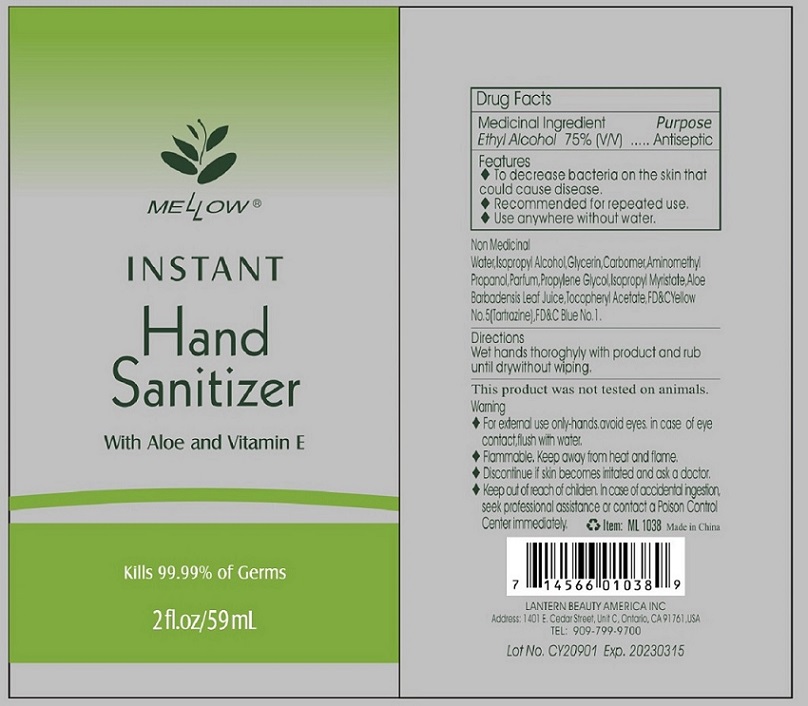 DRUG LABEL: Mellow Instant Hand Sanitizer 2 oz
NDC: 70108-034 | Form: GEL
Manufacturer: Ashtel Studios, Inc
Category: otc | Type: HUMAN OTC DRUG LABEL
Date: 20200408

ACTIVE INGREDIENTS: ALCOHOL 75 mL/100 mL
INACTIVE INGREDIENTS: WATER; ISOPROPYL ALCOHOL; GLYCERIN; CARBOMER HOMOPOLYMER, UNSPECIFIED TYPE; AMINOMETHYLPROPANOL; PROPYLENE GLYCOL; ISOPROPYL MYRISTATE; ALOE VERA LEAF; .ALPHA.-TOCOPHEROL ACETATE; FD&C YELLOW NO. 5; FD&C BLUE NO. 1

MELLOW INSTANT Hand Sanitizer

Medicinal Ingredient

Ethyl Alcohol 75% (V/V)

Purpose

Antiseptic

Features

♦ To decrease bacteria on the skin that could cause disease.

♦ Recommended for repeated use.

♦ Use anywhere without water.

Non Medicinal

Water, Isopropyl Alcohol, Glycerin, Carbomer, Aminomethyl Propanol, Parfum, Propylene Glycol, Isopropyl Myristate, Aloe Barbadensis Leaf Juice, Tocopheryl Acetate, FD&C Yellow No. 5(Tartrazine), FD&C Blue No.1.

Directions

Wet hands thoroughly with product and rub until dry without wiping.

Warning

♦ For external use only-hands, avoid eyes, in case of eye contact flush with water

♦ Flammable. Keep away from heat and flame.

♦ Discontinue if skin becomes irritated and ask a doctor.

Keep out of reach of children

In case of accidental ingestion, seek professional assistance or contact a Poison Control Center immediately.

With Aloe and Vitamin E

Kills 99.99% of Germs

This product was not tested on animals.

Made in China

LANTERN BEAUTY AMERICA INC

Address: 1401 E, Cedar Street, Unit C, Ontario, CA 91761, USA

TEL: 909-799-9700

Lot No. CY 20901 Exp. 20230315